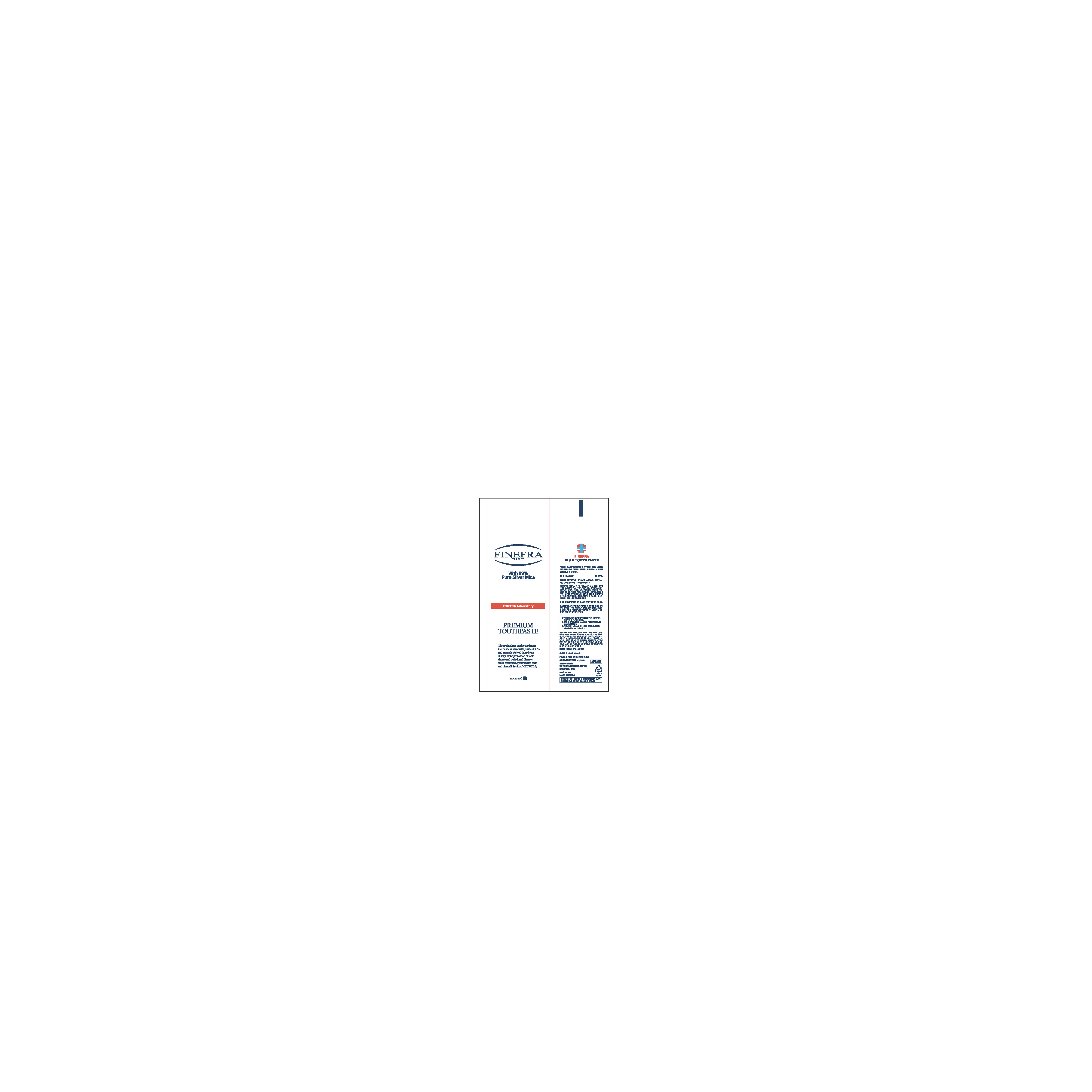 DRUG LABEL: BIS II Tooth
NDC: 69653-200 | Form: PASTE, DENTIFRICE
Manufacturer: Jewoo Medical CO.,LTD
Category: otc | Type: HUMAN OTC DRUG LABEL
Date: 20260203

ACTIVE INGREDIENTS: DIBASIC CALCIUM PHOSPHATE DIHYDRATE 0.04 g/100 g; CALCIUM CARBONATE 0.1 g/100 g; ALCLOXA 0.04 g/100 g; .ALPHA.-TOCOPHEROL ACETATE 0.04 g/100 g
INACTIVE INGREDIENTS: WATER; GLYCERIN

Drug Facts

ACTIVE INGREDIENT

Precipitated Calcium Carbonate
Tocopherol Acetate
Dibasic Calcium Phosphate Hydrate
Aluminium Chlorohydroxy Allantoinate

INACTIVE INGREDIENT

Glycerin
D-Sorbitol Solution
Silica
Carboxymethylcellulose Sodium
Sodium Cocoyl Glycinate
Mica
Chitosan
Xylitol
Steviol Glycoside
L-Menthol
Glycyrrhiza Extract
Sophora Flavescens Extract
Scutellaria Baicalensis Root Extract
Salvia Officinalis (Sage) Extract
Calendula Officinalis Flower Extract
Gentiana Lutea Root Extract
Rosmarinus Officinalis (Rosemary) Extract
Aloe Barbadensis Leaf Extract
Citrus Paradisi (Grapefruit) Seed Extract
Lavandula Angustifolia (Lavender) Extract
Propolis Extract
Eucalyptus Globulus Leaf Oil
Chamaecyparis Obtusa Oil
Pistacia Lentiscus (Mastic) Gum
Anethole
fravor
Silver
Activated Carbon
Hydroxyapatite
Water

PURPOSE

Aids in the prevention of cavities, plaque, and gingivitis

keep out of reach of the children

INDICATIONS AND USAGE

Adults and children 2 yrs. older: Brush teeth thoroughly after meals or at least twice a day, or use as directed by a tentist or physician. Do not shallow.

Children under 6 yrs.: To minimize swallowing, use a pea-sized amount and supervise brushing until good habits are established.

Children under 2 yrs.: Ask a dentist or physician.

Keep out of reach of children under 6 years of age.

If you accidentally swallow more than used for brushing, seek professional help or contact a poison control center immediately.

DOSAGE AND ADMINISTRATION

for external use only